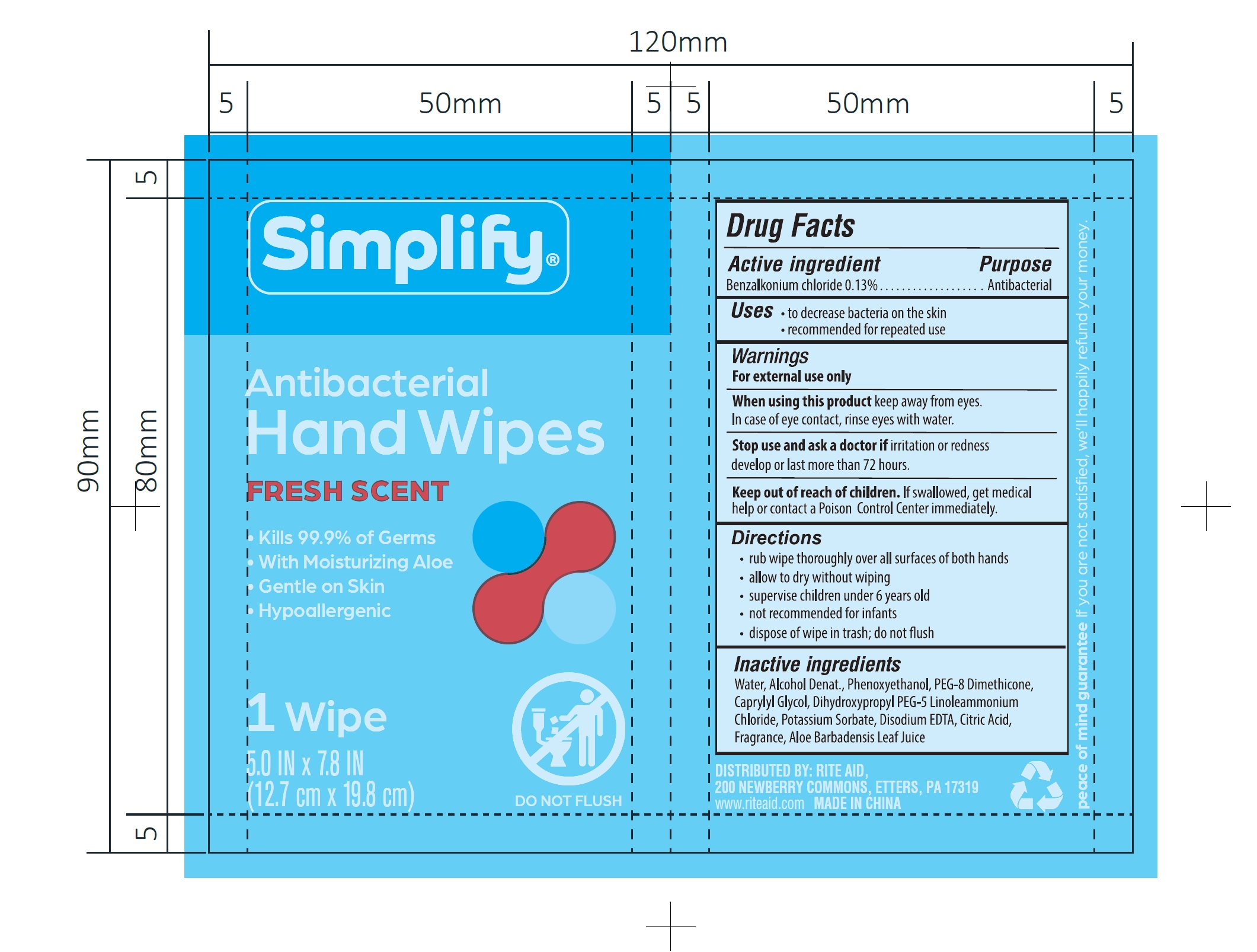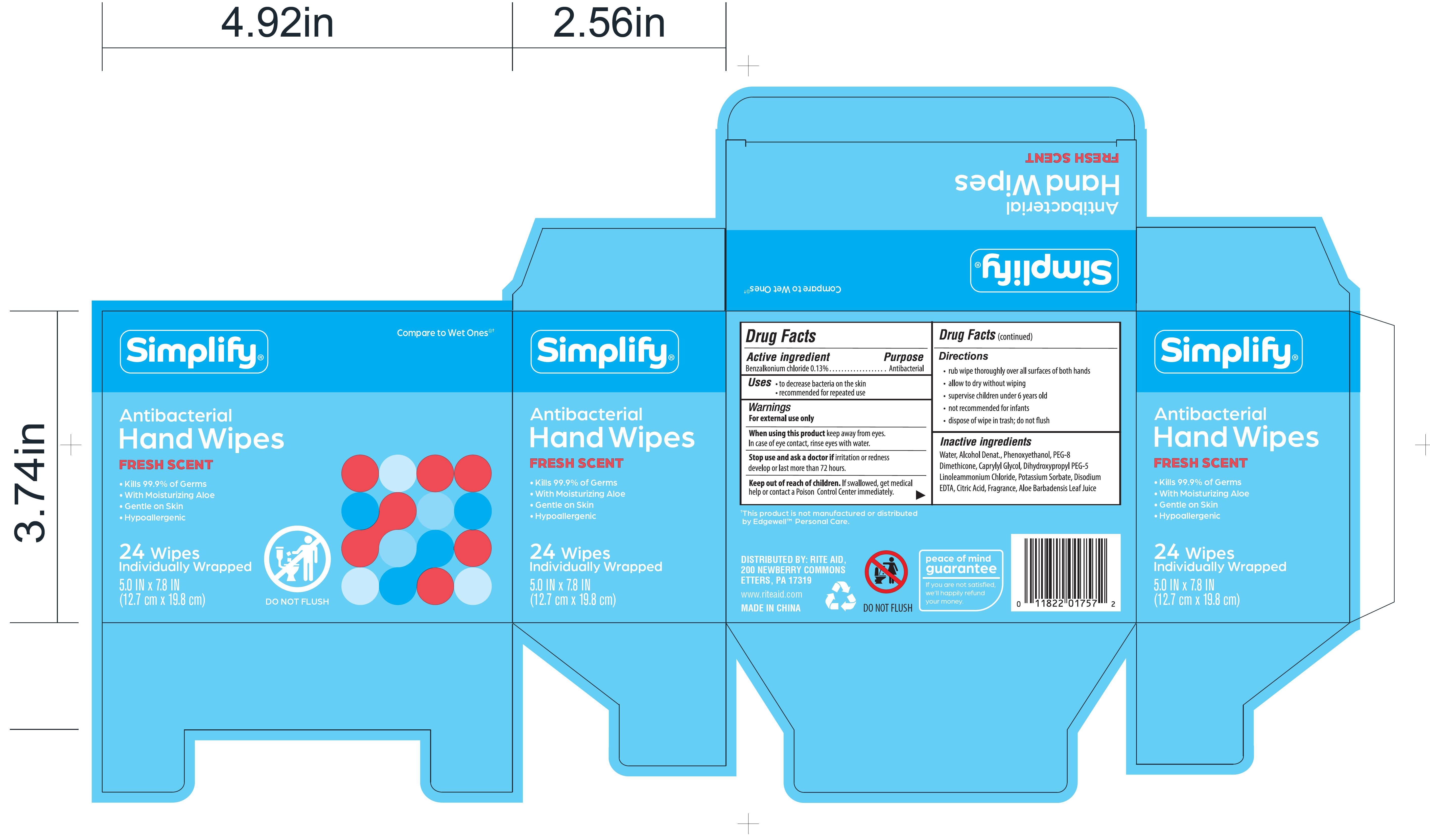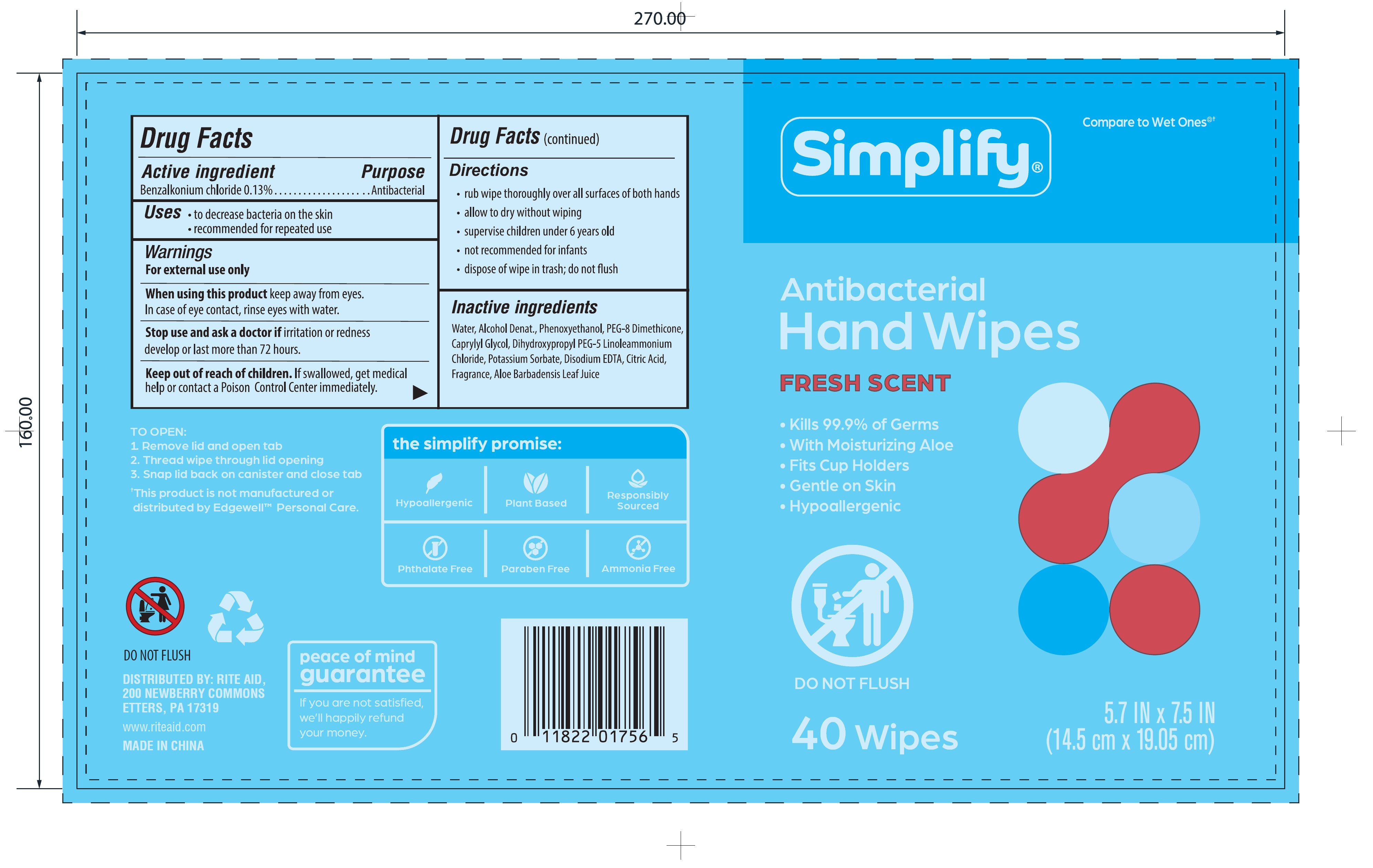 DRUG LABEL: Simplify Antibacterial Hand Wipes
NDC: 11822-0286 | Form: CLOTH
Manufacturer: RITE AID CORPORATION
Category: otc | Type: HUMAN OTC DRUG LABEL
Date: 20251217

ACTIVE INGREDIENTS: BENZALKONIUM CHLORIDE 0.13 g/100 g
INACTIVE INGREDIENTS: CAPRYLYL GLYCOL; DIHYDROXYPROPYL PEG-5 LINOLEAMMONIUM CHLORIDE; CITRIC ACID MONOHYDRATE; POTASSIUM SORBATE; WATER; ALOE VERA LEAF; PHENOXYETHANOL; ALCOHOL; PEG-8 DIMETHICONE; EDETATE DISODIUM

11822-0286 Simplify Antibacterial Hand Wipes

Active ingredient

Benzalkonium chloride 0.13%

Purpose

Antibacterial

INDICATIONS AND USAGE

Uses · to decrease bacteria on the skin

· recommended for repeated use

Warnings

For external use only

When using this product keep away from eyes.

In case of eye contact, rinses eyes with water.

Stop use and ask a doctor if irritation or redness

develop or last more than 72 hours.

KEEP OUT OF REACH OF CHILDREN

Keep out of the reach of children. If swallowed, get medical

help or contact a Poison Control Center immediately.

Directions

· rub wipe thoroughly over all surfaces of both hands

· allow to dry without wiping

· supervise children under 6 years old

· not recommended for infants

· dispose of wipe in trash; do not flush

Inactive ingredients

Water, Alcohol Denat., Phenoxyethanol, PEG-8 Dimethicone, Caprylyl Glycol, Dihydroxypropyl PEG-5 Linoleammonium Chloride, Potassium Sorbate, Disodium EDTA, Citric Acid, Fragrance, Aloe Barbadensis Leaf Juice

PACKAGE LABEL

1 Wipe
5.0 IN × 7.8 IN
(12.7 cm × 19.8 cm)
NDC: 11822-0286-1

24 Wipes
Individually Wrapped
5.0 IN × 7.8 IN
(12.7 cm × 19.8 cm)
NDC: 11822-0286-2

PACKAGE LABEL

40 Wipes
5.7 IN × 7.5 IN
(14.5 cm × 19.05 cm)
NDC: 11822-0286-3